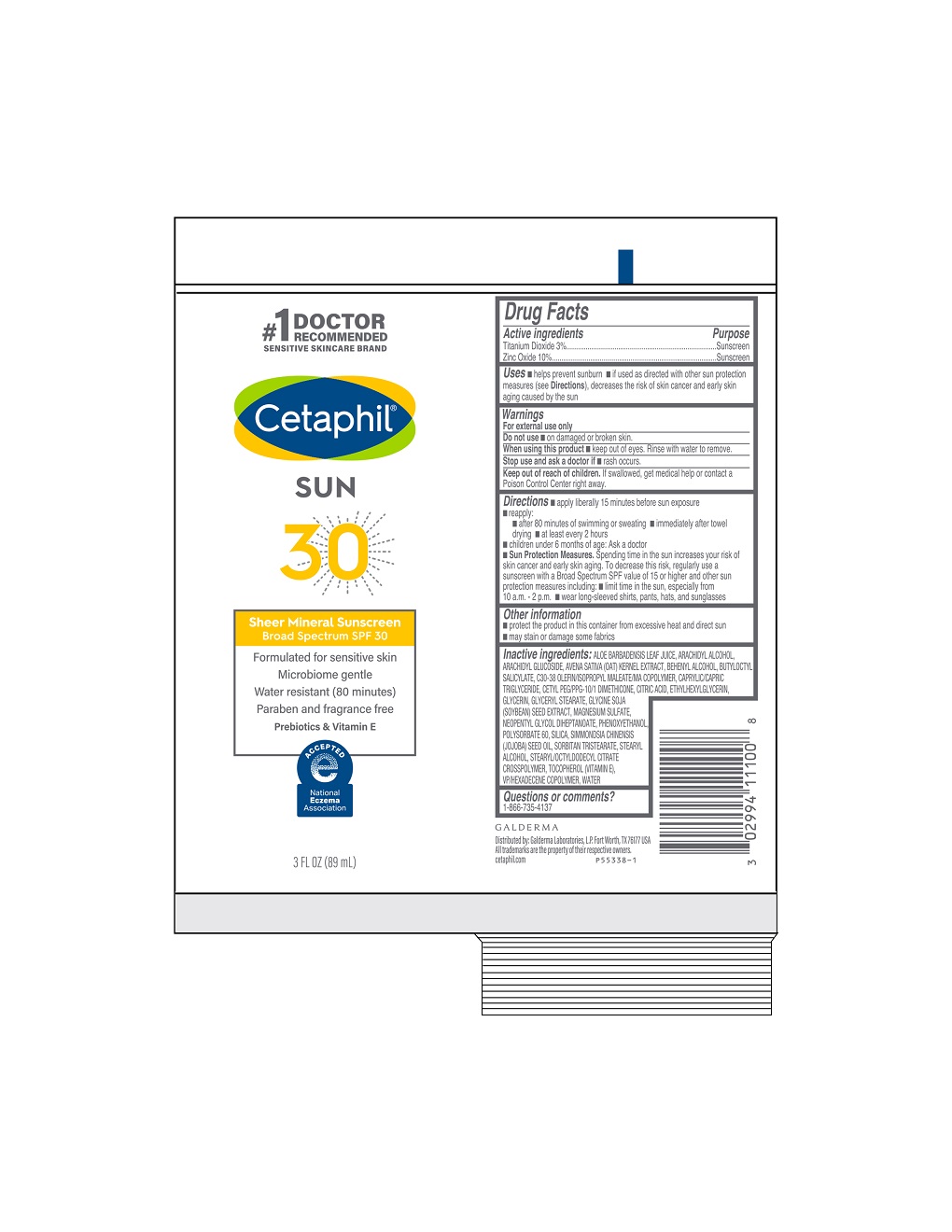 DRUG LABEL: Cetaphil Sheer Mineral Sunscreen SPF 30
NDC: 0299-4111 | Form: LOTION
Manufacturer: Galderma Laboratories, L.P.
Category: otc | Type: HUMAN OTC DRUG LABEL
Date: 20231207

ACTIVE INGREDIENTS: Titanium Dioxide 30 mg/1 mL; Zinc Oxide 100 mg/1 mL
INACTIVE INGREDIENTS: Aloe Vera Leaf; Arachidyl Alcohol; Arachidyl Glucoside; Oat; Docosanol; Butyloctyl Salicylate; Medium-Chain Triglycerides; Cetyl Peg/Ppg-10/1 Dimethicone (Hlb 2); Citric Acid Monohydrate; Ethylhexylglycerin; Glycerin; Glyceryl Monostearate; Soybean; Magnesium Sulfate, Unspecified Form; Neopentyl Glycol Diheptanoate; Phenoxyethanol; Polysorbate 60; Silicon Dioxide; Jojoba Oil; Sorbitan Tristearate; Stearyl Alcohol; Stearyl/Octyldodecyl Citrate Crosspolymer; Tocopherol; Vinylpyrrolidone/Hexadecene Copolymer; Water

Cetaphil Sheer Mineral Sunscreen Broad Spectrum SPF 30

Active Ingredients

Titianium Dioxide 3%
Zinc Oxide 10%

Purpose

Sunscreen

Uses

- helps prevent sunburn
- if used as directed with other sun protection measures (see Directions), decreases the risk of skin cancer and early skin aging caused by the sun

Do not use

▪ on damaged or broken skin

When using this product

• keep out of eyes. Rinse with water to remove.

Stop use and ask a doctor if

• rash occurs.

Keep out of reach of children.

If swallowed, get medical help or contact a Poison Control Center right away.

Directions

- apply liberally 15 minutes before sun exposure
- reapply:
  - after 80 minutes of swimming or sweating
  - immediately after towel drying
  - at least every 2 hours
- children under 6 months of age: Ask a doctor
- Sun Protection Measures. Spending time in the sun increases your risk of skin cancer and early skin aging. To decrease this risk, regularly use a sunscreen with a Broad Spectrum SPF value of 15 or higher and other sun protection measures including:
  - limit time in the sun, especially from 10 a.m. - 2 p.m.
  - wear long-sleeved shirts, pants, hats, and sunglasses

Other Information
protect the product in this container from excessive heat and direct sun, may stain or damage some fabrics

Inactive Ingredients

ALOE BARBADENSIS LEAF JUICE, ARACHIDYL ALCOHOL, ARACHIDYL GLUCOSIDE, AVENA SATIVA (OAT) KERNEL EXTRACT, BEHENYL ALCOHOL, BUTYLOCTYL SALICYLATE, C30-38 OLEFIN/ISOPROPYL MALEATE/MA COPOLYMER, CAPRYLIC/CAPRIC TRIGLYCERIDE, CETYL PEG/PPG-10/1 DIMETHICONE, CITRIC ACID, ETHYLHEXYLGLYCERIN, GLYCERIN, GLYCERYL STEARATE, GLYCINE SOJA (SOYBEAN) SEED EXTRACT, MAGNESIUM SULFATE, NEOPENTYL GLYCOL DIHEPTANOATE, PHENOXYETHANOL, POLYSORBATE 60, SILICA, SIMMONDSIA CHINENSIS (JOJOBA) SEED OIL, SORBITAN TRISTEARATE, STEARYL ALCOHOL, STEARYL/OCTYLDODECYL CITRATE CROSSPOLYMER, TOCOPHEROL (VITAMIN E), VP/HEXADECENE COPOLYMER, WATER

Questions or comments?

1-866-735-4137

PRINCIPAL DISPLAY PANEL - 3 FL OZ TUBE

#1 Doctor Recommended
Sensitive Skincare Brand

Cetaphil®

SUN
30

Sheer Mineral Sunscreen

Broad Spectrum SPF 30

Formulated for sensitive skin

Microbiome gentle

Water resistant (80 minutes)
Paraben and fragrance free
Prebiotics & Vitamin E

National Eczema Association logo

3 FL OZ (89 mL)

Dist. by:

Galderma Laboratories, L.P.

Fort Worth, TX 76177 USA

All trademarks are the property of their respective owners.

cetaphil.com
P55338-1